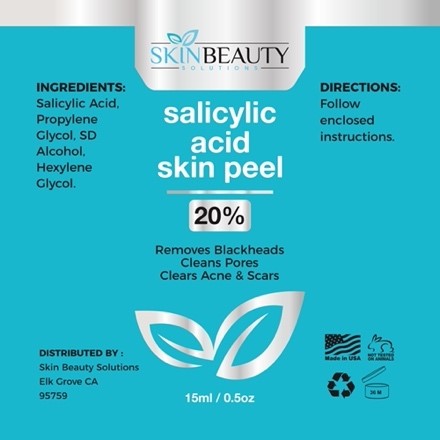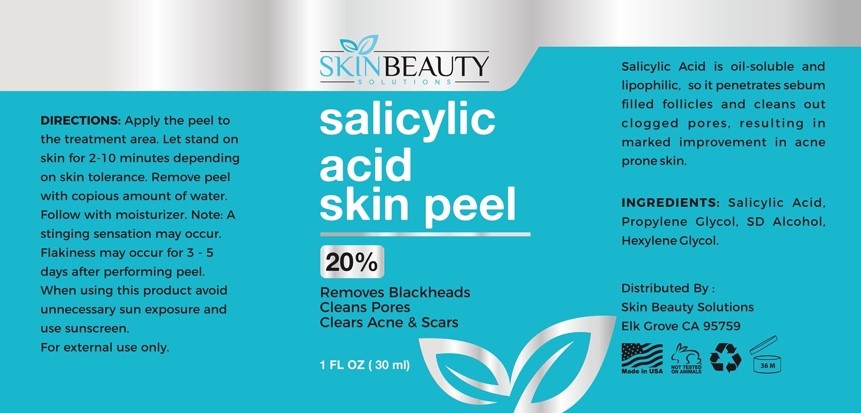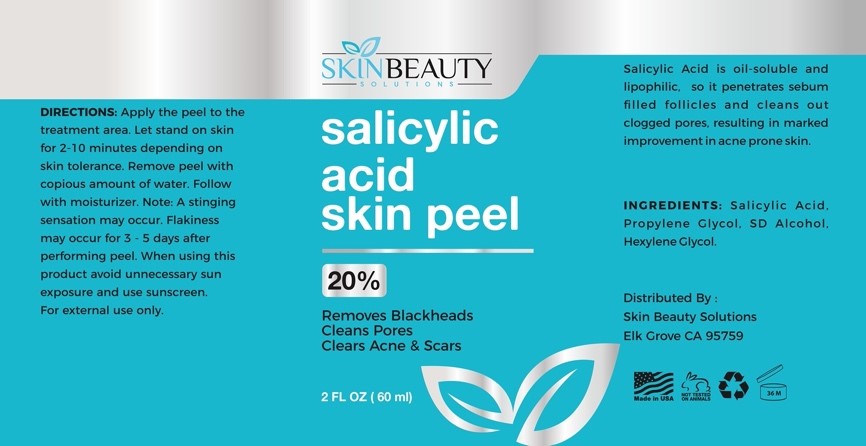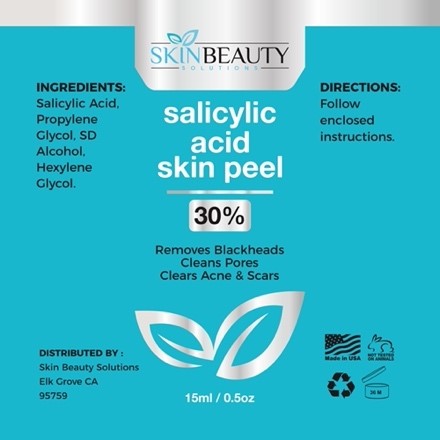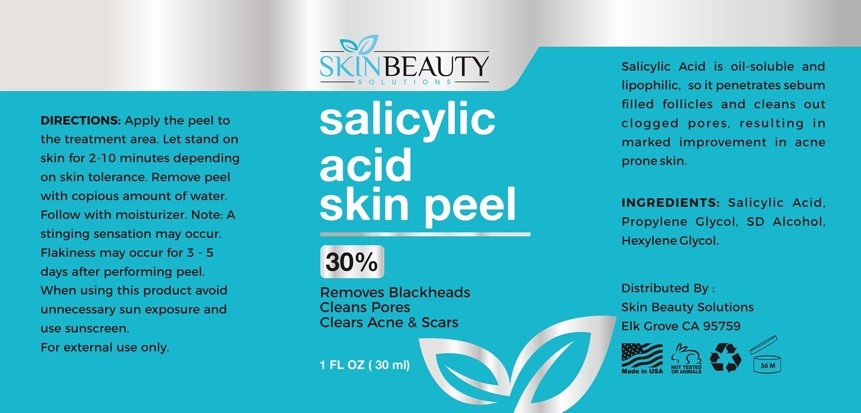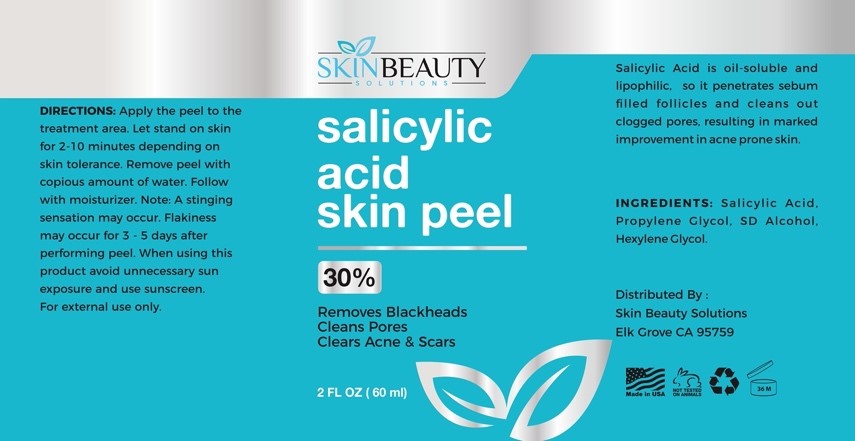 DRUG LABEL: SALICYLIC 20 Skin Peel
NDC: 84785-0013 | Form: SOLUTION
Manufacturer: Gazebo Wellness SKIN LLC
Category: otc | Type: HUMAN OTC DRUG LABEL
Date: 20241216

ACTIVE INGREDIENTS: SALICYLIC ACID 0.3 mg/30 mL
INACTIVE INGREDIENTS: HEXYLENE GLYCOL; CITRAL PROPYLENE GLYCOL ACETAL; ALCOHOL

DOSAGE AND ADMINISTRATION

Note: A stinging sensation may occur. Flakiness may occur for 3-5 days after performing peel. When using this product avoid unnecessary sun exposure and

WARNINGS

DIRECTIONS: Apply the peel to the treatment area. Let stand on skin for 2-10 minutes depending on skin tolerance. Remove peel with copious amount of water. Follow with moisturizer. Note: A stinging sensation may occur. Flakiness may occur for 3-5 days after performing peel. When using this product avoid unnecessary sun exposure and

Inactive ingredients: Propylene Glycol, SD Alcohol, Hexylene Glycol.

Active ingredient: Salicylic Acid.

keep out of reach of children

INDICATIONS AND USAGE

Apply the peel to the treatment area. Let stand on skin for 2-10 minutes depending on skin tolerance. Remove peel with copious amount of water. Follow with moisturizer. Note: A stinging sensation may occur. Flakiness may occur for 3-5 days after performing peel. When using this product avoid unnecessary sun exposure and
use sunscreen.
For external use only.

PURPOSE

salicylic acid skin peel
20%
Removes Blackheads Cleans Pores
Clears Acne & Scars

Distributed By:
Skin Beauty Solutions Elk Grove CA 95759

PACKAGE LABEL

Content of labeing